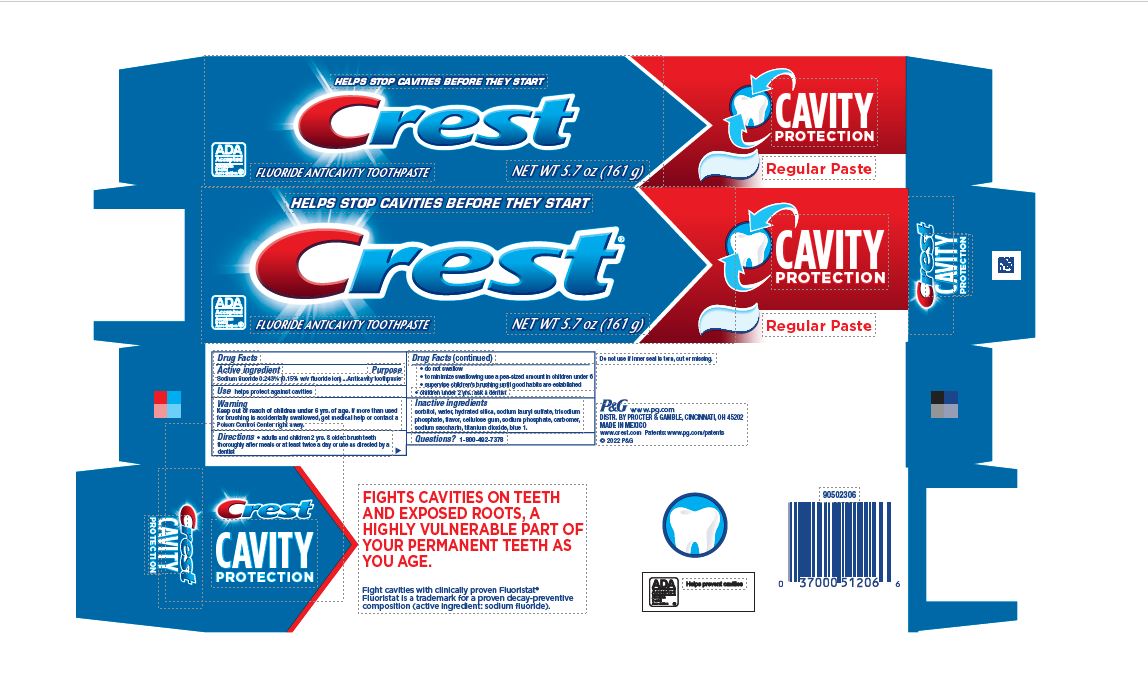 DRUG LABEL: Crest Cavity Protection
NDC: 58933-005 | Form: PASTE, DENTIFRICE
Manufacturer: Procter & Gamble Manufactura, S. de R.L. de C.V.
Category: otc | Type: HUMAN OTC DRUG LABEL
Date: 20260205

ACTIVE INGREDIENTS: SODIUM FLUORIDE 1.5 mg/1 g
INACTIVE INGREDIENTS: SORBITOL; WATER; HYDRATED SILICA; SODIUM LAURYL SULFATE; SODIUM PHOSPHATE; CARBOXYMETHYLCELLULOSE SODIUM; SACCHARIN SODIUM; TITANIUM DIOXIDE; FD&C BLUE NO. 1

Crest® Cavity Protection
Regular Paste

Active Ingredient

Sodium fluoride 0.243% (0.15% w/v fluoride ion)

Purpose

Anticavity toothpaste

Use

helps protect teeth and roots against cavities

Warnings

Keep out of reach of children under 6 yrs. of age. If more than used for brushing is accidentally swallowed, get medical help or contact a Poison Control Center right away.

Keep out of reach of children under 6 yrs. of age. If more than used for brushing is accidentally swallowed, get medical help or contact a Poison Control Center right away.

Directions

- adults and children 2 yrs. & older: brush teeth thoroughly after meals or at least twice a day or use as directed by a dentist
- do not swallow
- to minimize swallowing use a pea-sized amount in childrenunder 6
- supervise children’s brushing until good habits are established
- children under 2 yrs.: ask a dentist

Inactive ingredients

sorbitol, water, hydrated silica, sodium lauryl sulfate, trisodium phosphate, flavor, sodium phosphate, cellulose gum, carbomer, sodium saccharin, titanium dioxide, blue 1

Questions?

1-800-492-7378

Dist. by Procter & Gamble,
Cincinnati, OH 45202

PRINCIPAL DISPLAY PANEL - 161 g Tube Carton

HELPS STOP CAVITIES BEFORE THEY START

Crest®

CAVITY
PROTECTION

ADA
Accepted
American
Dental
Association®

FLUORIDE ANTICAVITY TOOTHPASTE

NET WT 5.7 OZ (161 g)

Regular Paste